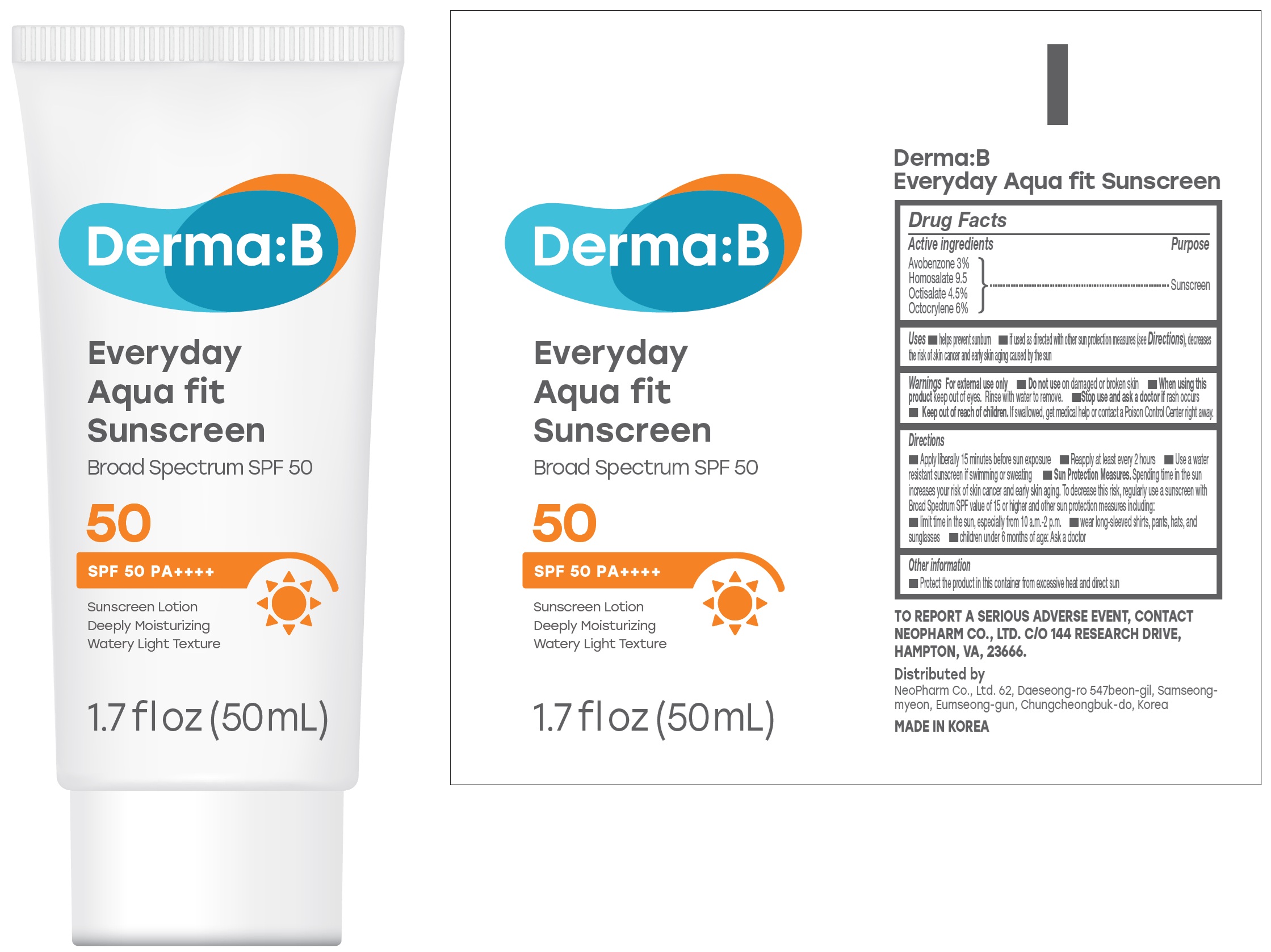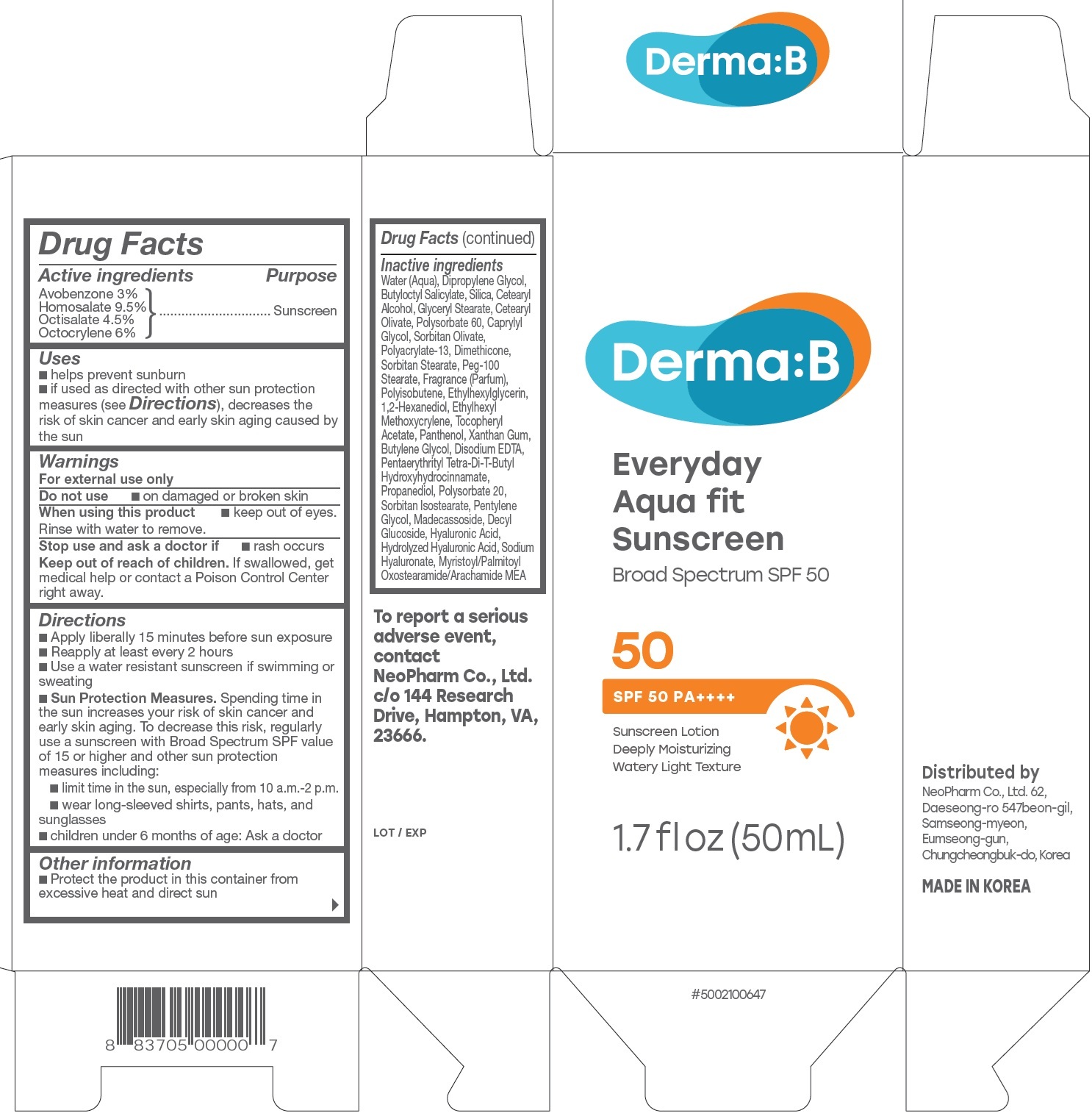 DRUG LABEL: Derma B Everyday Fit Sunscreen SPF 50
NDC: 51141-0701 | Form: LOTION
Manufacturer: NeoPharm Co., Ltd.
Category: otc | Type: HUMAN OTC DRUG LABEL
Date: 20260204

ACTIVE INGREDIENTS: AVOBENZONE 30 mg/1 mL; HOMOSALATE 95 mg/1 mL; OCTISALATE 45 mg/1 mL; OCTOCRYLENE 60 mg/1 mL
INACTIVE INGREDIENTS: HYALURONIC ACID; HYALURONATE SODIUM; MYRISTOYL/PALMITOYL OXOSTEARAMIDE/ARACHAMIDE MEA; WATER; DIPROPYLENE GLYCOL; BUTYLOCTYL SALICYLATE; SILICON DIOXIDE; CETOSTEARYL ALCOHOL; GLYCERYL MONOSTEARATE; CETEARYL OLIVATE; POLYSORBATE 60; CAPRYLYL GLYCOL; SORBITAN OLIVATE; POLYACRYLATE-13; DIMETHICONE; SORBITAN STEARATE; PEG-100 MONOSTEARATE; ETHYLHEXYLGLYCERIN; 1,2-HEXANEDIOL; ETHYLHEXYL METHOXYCRYLENE; .ALPHA.-TOCOPHEROL ACETATE; PANTHENOL; XANTHAN GUM; BUTYLENE GLYCOL; EDETATE DISODIUM; PENTAERYTHRITOL TETRAKIS(3-(3,5-DI-TERT-BUTYL-4-HYDROXYPHENYL)PROPIONATE); PROPANEDIOL; POLYSORBATE 20; SORBITAN ISOSTEARATE; PENTYLENE GLYCOL; MADECASSOSIDE; DECYL GLUCOSIDE

Derma: B Everyday Aqua Fit Sunscreen SPF 50

Active ingredients

Avobenzone 3%
Homosalate 9.5
Octisalate 4.5%
Octocrylene 6%

Purpose

Sunscreen

Uses

- helps prevent sunburn
- if used as directed with other sun protection measures (see Directions), decreases the risk of skin cancer and early skin aging caused by the sun

Warnings

For external use only

Do not use

- on damaged or broken skin

When using this product

- keep out of eyes. Rinse with water to remove.

Stop use and ask a doctor if

- rash occurs

Keep out of reach of children.

- If swallowed, get medical help or contact a Poison Control Center right away.

Directions

• Apply liberally 15 minutes before sun exposure • Reapply at least every 2 hours • Use a water resistant sunscreen if swimming or sweating • Sun Protection Measures.Spending time in the sun increases your risk of skin cancer and early skin aging. To decrease this risk, regularly use a sunscreen with Broad Spectrum SPF value of 15 or higher and other sun protection measures including: • limit time in the sun, especially from 10 a.m.-2 p.m. • wear long-sleeved shirts, pants, hats, and sunglasses • children under 6 months of age: Ask a doctor

Other information

- Protect the product in this container from excessive heat and direct sun

Inactive ingredients

Water (Aqua), Dipropylene Glycol, Butyloctyl Salicylate, Silica, Cetearyl Alcohol, Glyceryl Stearate, Cetearyl Olivate, Polysorbate 60, Caprylyl Glycol, Sorbitan Olivate, Polyacrylate-13, Dimethicone, Sorbitan Stearate, Peg-100 Stearate, Fragrance (Parfum), Polyisobutene, Ethylhexylglycerin, 1,2-Hexanediol, Ethylhexyl Methoxycrylene, Tocopheryl Acetate, Panthenol, Xanthan Gum, Butylene Glycol, Disodium EDTA, Pentaerythrityl Tetra-Di-T-Butyl Hydroxyhydrocinnamate, Propanediol, Polysorbate 20, Sorbitan Isostearate, Pentylene Glycol, Madecassoside, Decyl Glucoside, Hyaluronic Acid, Hydrolyzed Hyaluronic Acid, Sodium Hyaluronate, Myristoyl/Palmitoyl Oxostearamide/Arachamide MEA